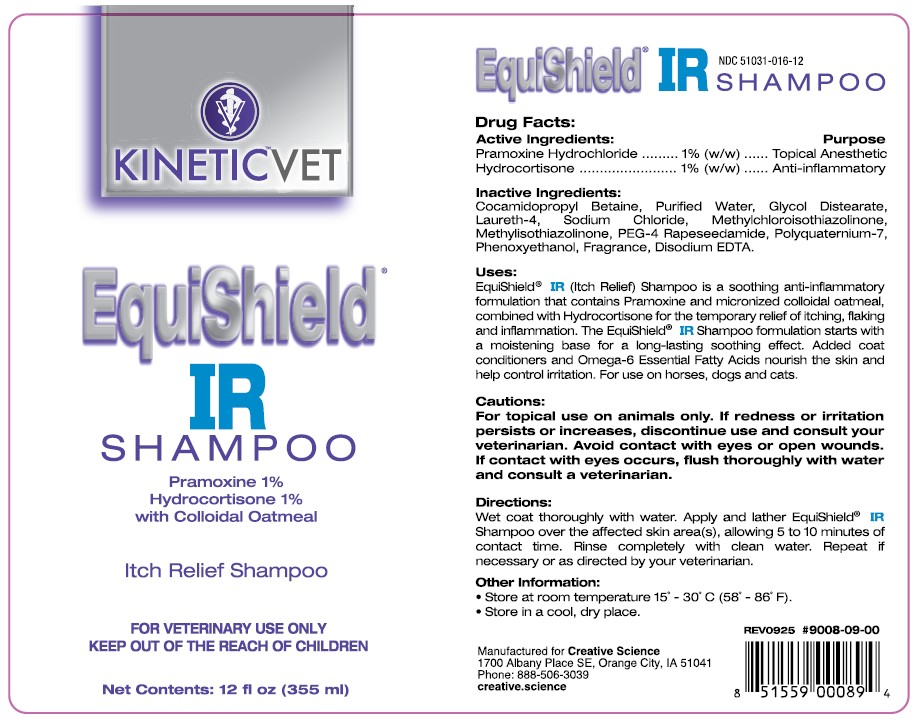 DRUG LABEL: EquiShield IR
NDC: 53413-016 | Form: SHAMPOO
Manufacturer: Creative Science
Category: animal | Type: OTC ANIMAL DRUG LABEL
Date: 20251231

ACTIVE INGREDIENTS: PRAMOXINE HYDROCHLORIDE 10 mg/1 mL; HYDROCORTISONE ACETATE 10 mg/1 mL

EquiShield® IR Shampoo

NDC 53413-016-12

Drug Facts:Active Ingredients:

Pramoxine Hydrochloride........... 1% (w/w)

Hydrocortisone......................... 1% (w/w)

Purpose

Topical Anesthetic

Anti-Inflammatory

Inactive Ingredients:

Cocamidopropyl Betaine, Purified Water, Glycol Distearate, Laureth-4, Sodium Chloride, Methylchloroisothiazolinone, Methylisothiazolinone, PEG-4 Rapeseedamide, Polyquaternium-7, Phenosyethanol, Fragrance, Disodium EDTA.

Uses:

EquiShield IR (Itch Relief) Shampoo is a soothing anti-inflammatory formulation that contains Pramoxine and micronized colloidal oatmeal, combined with Hydrocortisone for the temporary relief of itching, flaking and inflammation. The EquiShield IR Shampoo formulation starts with a moistening base for a long-lasting soothing effect. Added coat conditioners and Omega-6 Essential Fatty Acids nourish the skin and help control irritation. For use on horses, dogs and cats.

Cautions:

For topical use on animals only. If redness or irritation persists or increases, discontinue use and consult your veterinarian. Avoid contact with eyes or open wounds. If contact with eyes occurs, flush thoroughly with water and consult a veterinarian.

Directions:

Wet coat thoroughly with water. Apply and lather EquiShield IR Shampoo over the affected skin area(s), allowing 5 to 10 minutes of contact time. Rinse completely with clean water. Repeat if necessary or as directed by your veterinarian.

Other Information:

• Store at room temperature 15˚ - 30˚C (58˚ - 86˚F).
• Store in a cool, dry place.

REV0925 #9008-09-00

UPC 851559000894

Manufactured for Creative Science

1700 Albany Place SE, Orange City, IA 51041

Phone: 888-506-3039

creative.science

PACKAGE LABEL

EquiShield®

IR

Shampoo

Pramoxine 1%

Hydrocortisone 1%

with Colloidal Oatmeal

Itch Relief Shampoo

FOR VETERINARY USE ONLY

KEEP OUT OF THE REACH OF CHILDREN

Net Contents: 12 fl oz (355 ml)